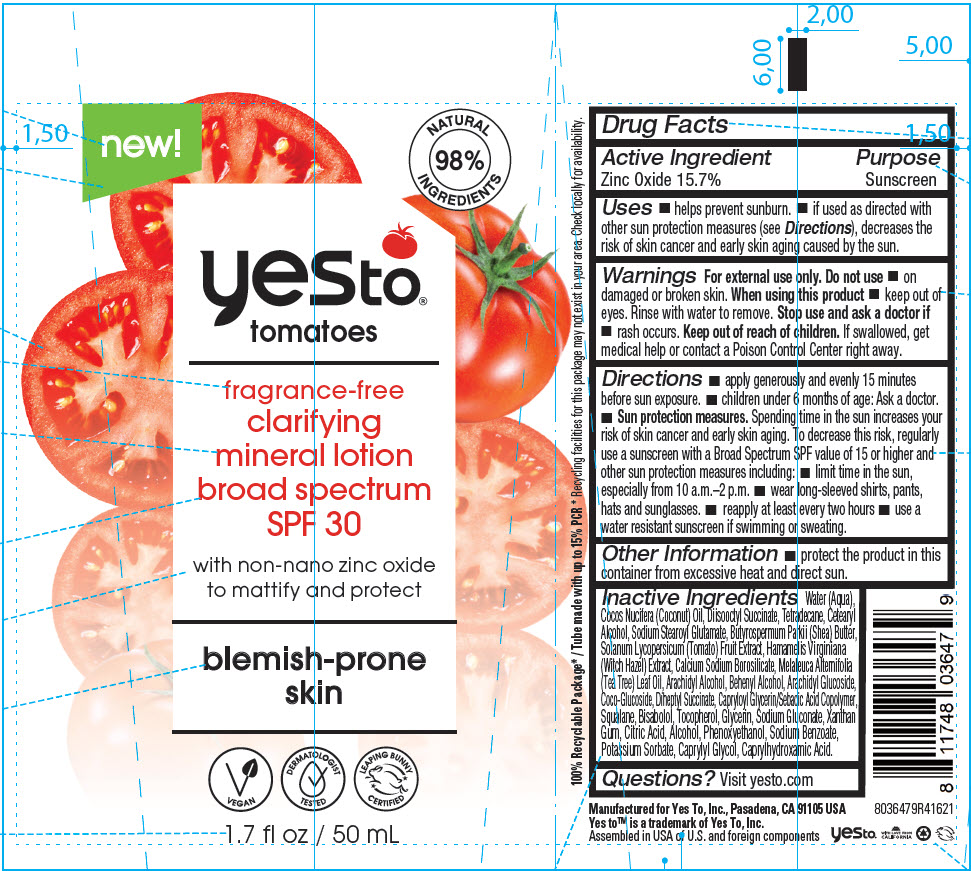 DRUG LABEL: Yes To Tomatoes Fragrance-Free Clarifying Mineral Broad Spectrum SPF-30
NDC: 69840-028 | Form: CREAM
Manufacturer: Yes To, Inc.
Category: otc | Type: HUMAN OTC DRUG LABEL
Date: 20220126

ACTIVE INGREDIENTS: Zinc Oxide 157 mg/1 mL
INACTIVE INGREDIENTS: Water; Sodium Gluconate; Sodium Benzoate; Potassium Sorbate; CITRIC ACID MONOHYDRATE; Alcohol; Xanthan Gum; HAMAMELIS VIRGINIANA TOP; TOMATO; Phenoxyethanol; Diheptyl Succinate; Sodium Stearoyl Glutamate; Caprylhydroxamic Acid; Caprylyl Glycol; Glycerin; COCONUT OIL; CAPRYLOYL GLYCERIN/SEBACIC ACID COPOLYMER (2000 MPA.S); Tetradecane; Squalane; SHEA BUTTER; .ALPHA.-BISABOLOL, (+/-)-; Tocopherol; TEA TREE OIL; CETOSTEARYL ALCOHOL; COCO GLUCOSIDE; Arachidyl Alcohol; DOCOSANOL; Arachidyl Glucoside

Yes To® Tomatoes Fragrance-Free Clarifying Mineral Lotion Broad Spectrum SPF-30

Drug Facts

Active Ingredient

Zinc Oxide 15.7%

Purpose

Sunscreen

Uses

- helps prevent sunburn.
- if used as directed with other sun protection measures (see Directions), decreases the risk of skin cancer and early skin aging caused by the sun.

Warnings

For external use only.

Do not use

- on damaged or broken skin.

When using this product

- keep out of eyes. Rinse with water to remove.

Stop use and ask a doctor if

- rash occurs.

Keep out of reach of children. If swallowed, get medical help or contact a Poison Control Center right away.

Directions

- apply generously and evenly 15 minutes before sun exposure.
- children under 6 months of age: Ask a doctor.
- Sun protection measures. Spending time in the sun increases your risk of skin cancer and early skin aging. To decrease this risk, regularly use a sunscreen with a Broad Spectrum SPF value of 15 or higher and other sun protection measures including:
  - limit time in the sun, especially from 10 a.m.–2 p.m.
  - wear long-sleeved shirts, pants, hats and sunglasses.
- reapply at least every two hours
- use a water resistant sunscreen if swimming or sweating.

Other Information

- protect the product in this container from excessive heat and direct sun.

Inactive Ingredients

Water (Aqua), Cocos Nucifera (Coconut) Oil, Diisooctyl Succinate, Tetradecane, Cetearyl Alcohol, Sodium Stearoyl Glutamate, Butyrospermum Parkii (Shea) Butter, Solanum Lycopersicum (Tomato) Fruit Extract, Hamamelis Virginiana (Witch Hazel) Extract, Calcium Sodium Borosilicate, Melaleuca Alternifolia (Tea Tree) Leaf Oil, Arachidyl Alcohol, Behenyl Alcohol, Arachidyl Glucoside, Coco-Glucoside, Diheptyl Succinate, Capryloyl Glycerin/Sebacic Acid Copolymer, Squalane, Bisabolol, Tocopherol, Glycerin, Sodium Gluconate, Xanthan Gum, Citric Acid, Alcohol, Phenoxyethanol, Sodium Benzoate, Potassium Sorbate, Caprylyl Glycol, Caprylhydroxamic Acid.

Questions?

Visit yesto.com

PRINCIPAL DISPLAY PANEL - 50 mL Tube Label

new!

NATURAL
98%
INGREDIENTS

yesto®
tomatoes

fragrance-free
clarifying
mineral lotion
broad spectrum
SPF 30

with non-nano zinc oxide
to mattify and protect

blemish-prone
skin

VEGAN

DERMATOLOGIST
TESTED

LEAPING BUNNY
CERTIFIED

1.7 fl oz / 50 mL